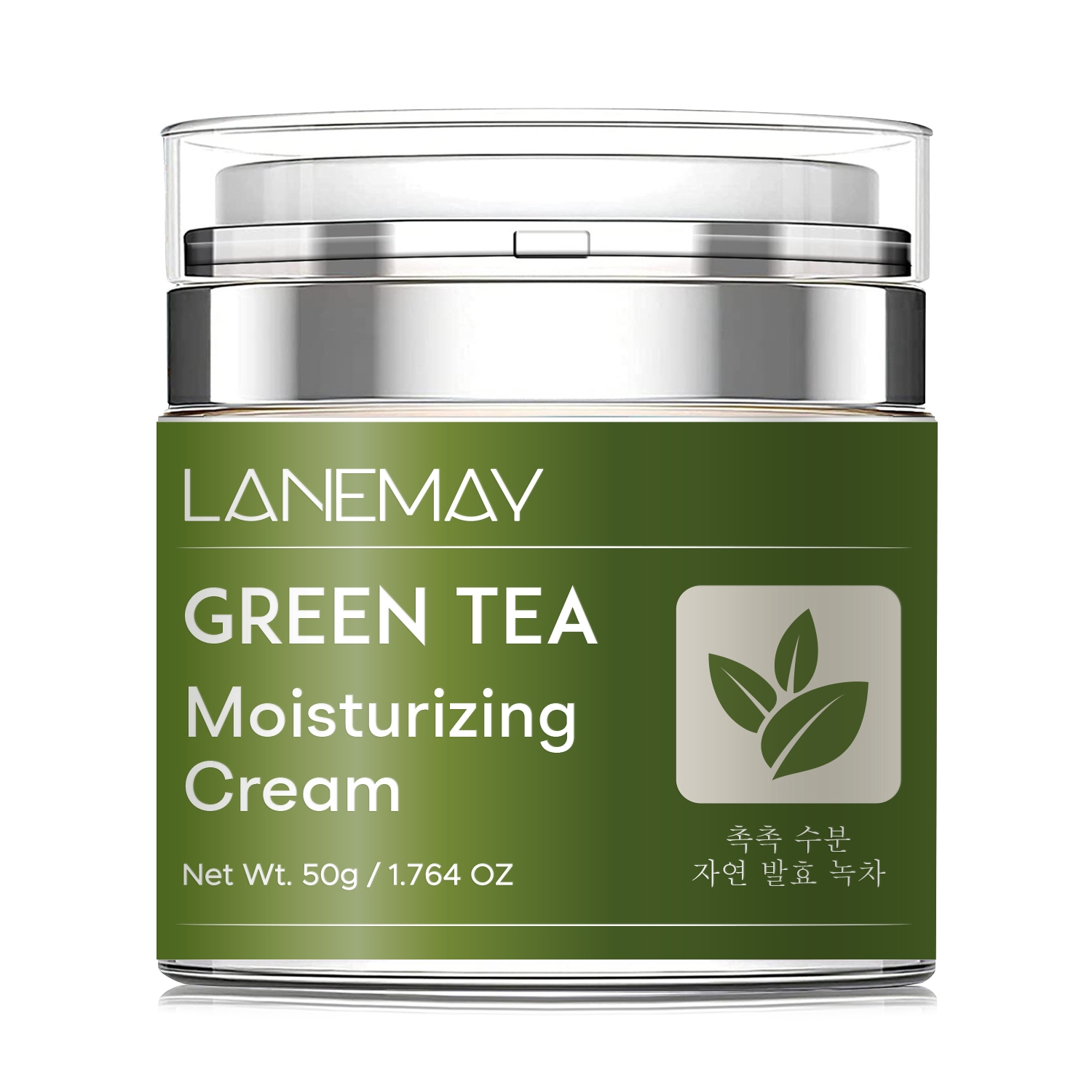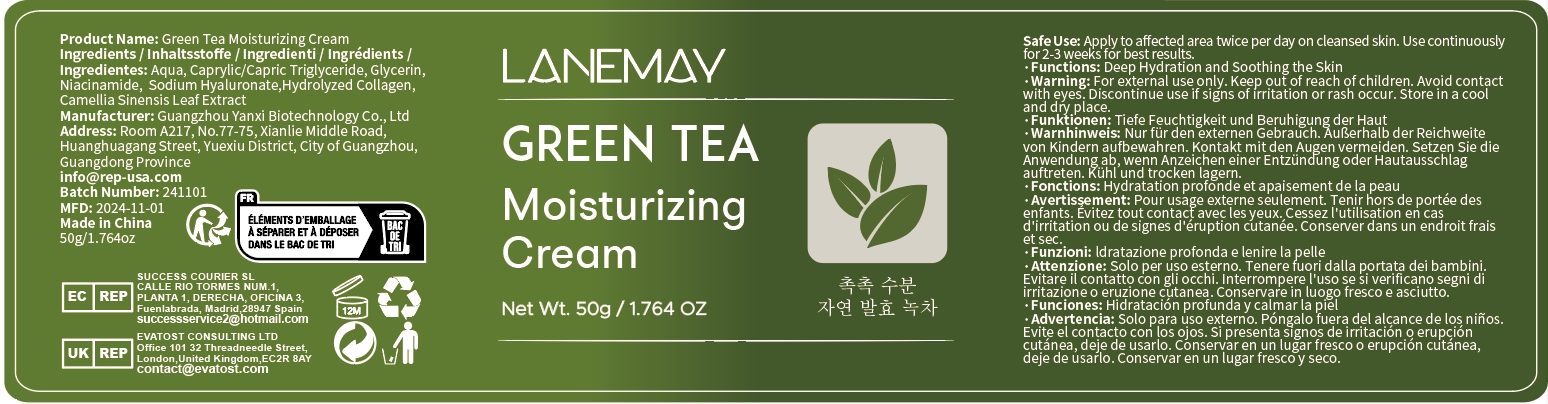 DRUG LABEL: Green Tea Moisturizing Cream
NDC: 84025-284 | Form: CREAM
Manufacturer: Guangzhou Yanxi Biotechnology Co., Ltd
Category: otc | Type: HUMAN OTC DRUG LABEL
Date: 20241219

ACTIVE INGREDIENTS: GLYCERIN 3 mg/50 g; NIACINAMIDE 2 mg/50 g
INACTIVE INGREDIENTS: WATER

DOSAGE AND ADMINISTRATION

Apply to affected area twice per day on cleansed skin.Use continuously for 2-3 weeks for best results.

WARNINGS

Keep out of children

INACTIVE INGREDIENT

Aqua

INDICATIONS AND USAGE

For daily skin care

Keep out of children

PURPOSE

Deep hydration and soothing the skin